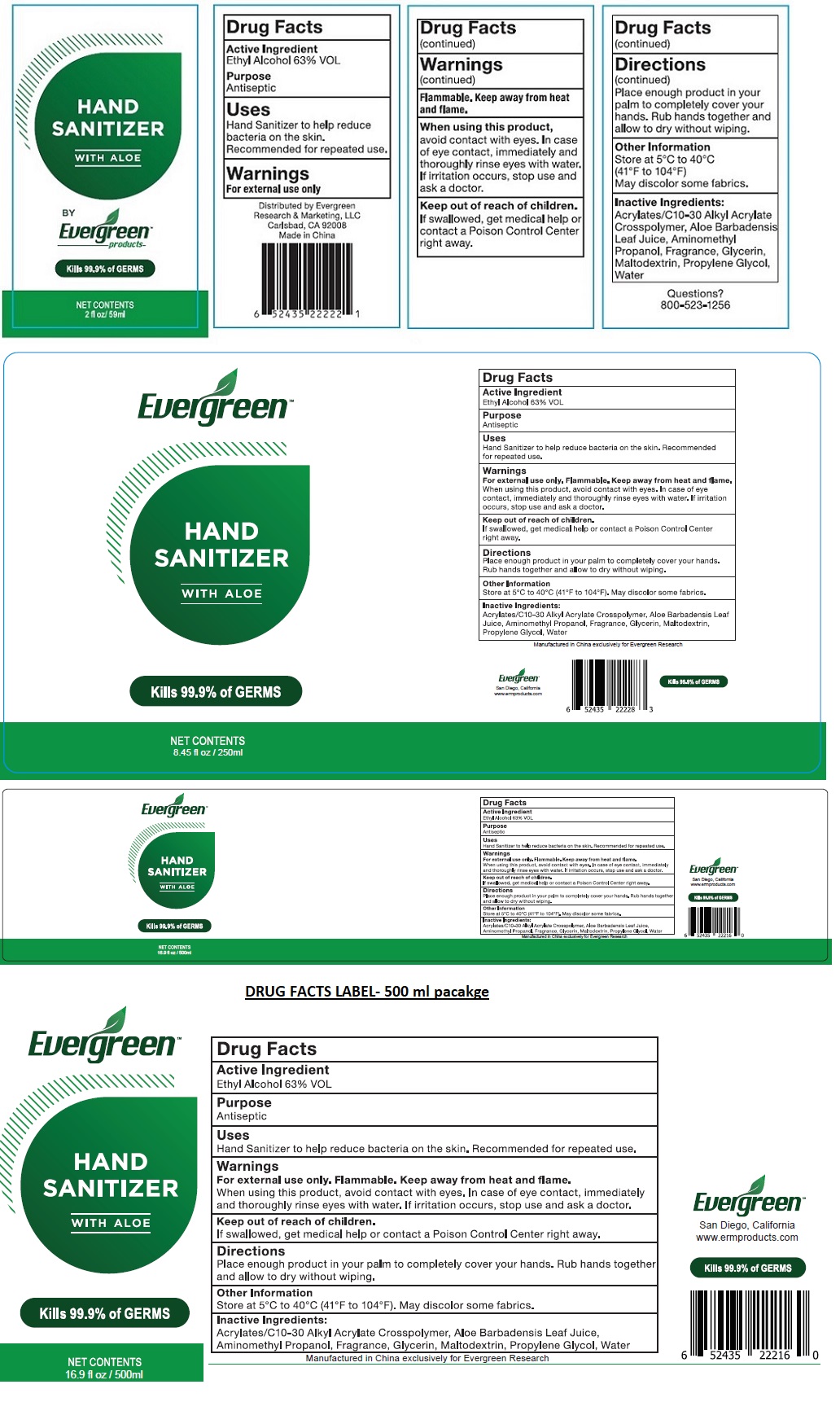 DRUG LABEL: Evergreen HAND SANITIZER
NDC: 75188-705 | Form: GEL
Manufacturer: Guangzhou Yucaitang Cosmetics Co., Ltd.
Category: otc | Type: HUMAN OTC DRUG LABEL
Date: 20200507

ACTIVE INGREDIENTS: ALCOHOL 63 mL/100 mL
INACTIVE INGREDIENTS: CARBOMER INTERPOLYMER TYPE A (ALLYL SUCROSE CROSSLINKED); ALOE VERA LEAF; AMINOMETHYLPROPANOL; GLYCERIN; MALTODEXTRIN; PROPYLENE GLYCOL; WATER

Evergreen HAND SANITIZER

Active Ingredient

Ethyl Alcohol 63% VOL

Purpose

Antiseptic

Uses

Hand Sanitizer to help reduce bacteria on the skin.
Recommended for repeated use.

Warnings

For external use only

Flammable. Keep away from heat and flame.

When using this product, avoid contact with eyes. In case of eye contact, immediately and thoroughly rinse eyes with water. If irritation occurs, stop use and ask a doctor.

Keep out of reach of children. If swallowed, get medical help or contact a Poison Control Center right away.

Directions

Place enough product in your palm to completely cover your hands. Rub hands together and allow to dry without wiping.

Other Information

Store at 5°C to 40°C (41°F to 104°F)

May discolor some fabrics.

Inactive Ingredients:

Acrylates/C10-30 Alkyl Acrylate Crosspolymer, Aloe Barbadensis Leaf Juice, Aminomethyl Propanol, Fragrance, Glycerin, Maltodextrin, Propylene Glycol, Water

WITH ALOE

Kills 99.9% of GERMS

Distributed by Evergreen

Research & Marketing, LLC

Carlsbad, CA 92008

Made in China

Questions?

800-523-1256